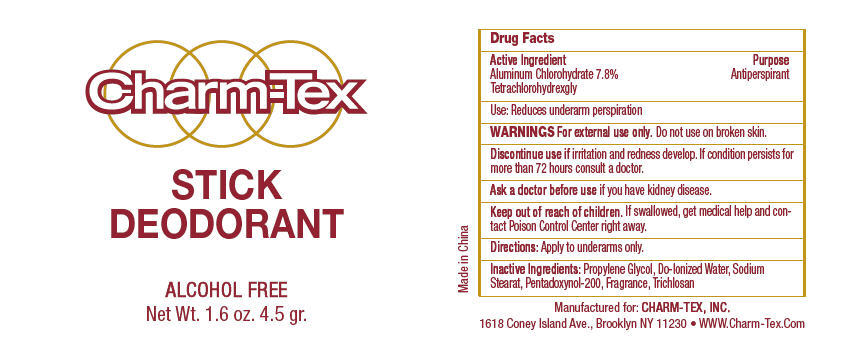 DRUG LABEL: Charm-Tex 
NDC: 40057-2000 | Form: STICK
Manufacturer: Charm-Tex, Inc.
Category: otc | Type: HUMAN OTC DRUG LABEL
Date: 20120119

ACTIVE INGREDIENTS: Aluminum chlorohydrate 7.8 g/100 g
INACTIVE INGREDIENTS: Propylene Glycol; Water; Sodium Stearate; Triclosan

Charm-Tex
STICK
DEODORANT

Drug Facts

Active Ingredient

Aluminum Chlorohydrate 7.8%

Tetrachlorohydrexgly

Purpose

Antiperspirant

Use

Reduces underarm perspiration

WARNINGS

For external use only.

Do not use on broken skin.

STOP USE

Discontinue use if irritation and redness develop. If condition persists for more than 72 hours consult a doctor.

Ask a doctor before use if you have kidney disease.

Keep out of reach of children. If swallowed, get medical help and contact Poison Control Center right away.

Directions

Apply to underarms only.

Inactive Ingredients

Propylene Glycol, Do-Ionized Water, Sodium Stearat, Pentadoxynol-200, Fragrance, Trichlosan

Manufactured for: CHARM-TEX, INC.
1618 Coney Island Ave., Brooklyn NY 11230

PRINCIPAL DISPLAY PANEL - 4.5 gr Applicator Label

Charm-Tex

STICK
DEODORANT

ALCOHOL FREE
Net Wt. 1.6 oz. 4.5 gr.